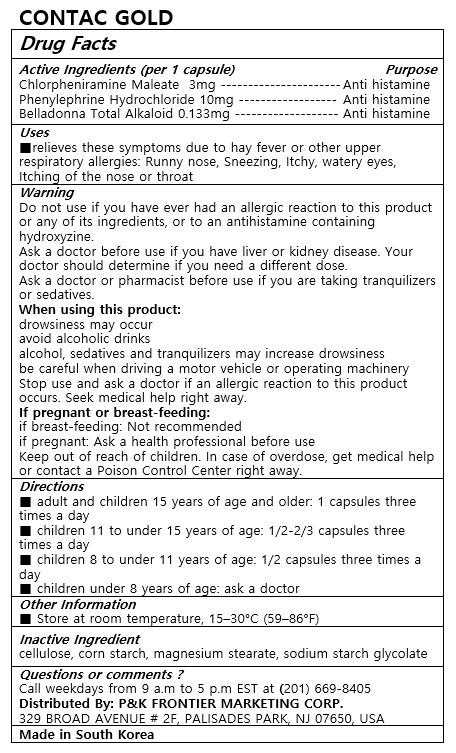 DRUG LABEL: CONTAC GOLD
NDC: 72689-0035 | Form: CAPSULE, COATED PELLETS
Manufacturer: OASIS TRADING
Category: otc | Type: HUMAN OTC DRUG LABEL
Date: 20190318

ACTIVE INGREDIENTS: PHENYLEPHRINE HYDROCHLORIDE 10 mg/1 1; CHLORPHENIRAMINE MALEATE 3 mg/1 1
INACTIVE INGREDIENTS: STARCH, CORN; ATROPA BELLADONNA ROOT 0.133 mg/1 1

ACTIVE INGREDIENT

Chlorpheniramine Maleate 3mg
Phenylephrine Hydrochloride 10mg
Belladonna Total Alkaloid 0.133mg

PURPOSE

■relieves these symptoms due to hay fever or other upper respiratory allergies:
Runny nose, Sneezing, Itchy, watery eyes, Itching of the nose or throat

Keep out of reach of children

INDICATIONS AND USAGE

■ adult and children 15 years of age and older: 1 capsules three times a day
■ children 11 to under 15 years of age: 1/2-2/3 capsules three times a day
■ children 8 to under 11 years of age: 1/2 capsules three times a day
■ children under 8 years of age: ask a doctor

WARNINGS

WARNING: Do not use if you have ever had an allergic reaction to this product or any of its ingredients, or to an antihistamine containing hydroxyzine.
Ask a doctor before use if you have liver or kidney disease. Your doctor should determine if you need a different dose.
Ask a doctor or pharmacist before use if you are taking tranquilizers or sedatives.
When using this product:
drowsiness may occur
avoid alcoholic drinks
alcohol, sedatives and tranquilizers may increase drowsiness
be careful when driving a motor vehicle or operating machinery
Stop use and ask a doctor if an allergic reaction to this product occurs. Seek medical help right away.
If pregnant or breast-feeding:
if breast-feeding: Not recommended
if pregnant: Ask a health professional before use

Keep out of reach of children. In case of overdose, get medical help or contact a Poison Control Center right away.
Store at room temperature, 15–30°C (59–86°F).

INACTIVE INGREDIENT

cellulose, corn starch, magnesium stearate, sodium starch glycolate

DOSAGE AND ADMINISTRATION

For oral use only